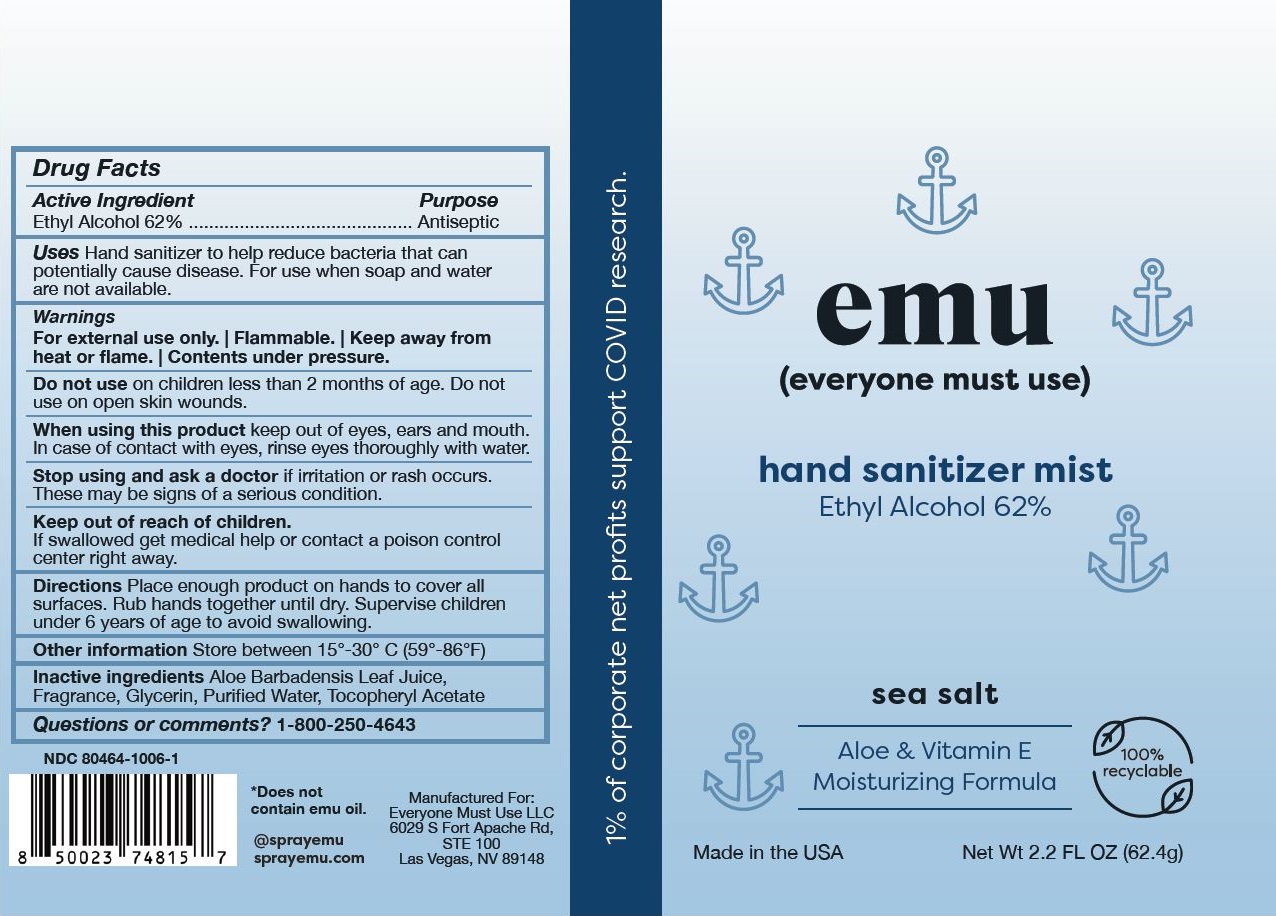 DRUG LABEL: Hand Sanitizer Mist Sea Salt
NDC: 80464-1006 | Form: SPRAY
Manufacturer: Everyone Must Use LLC
Category: otc | Type: HUMAN OTC DRUG LABEL
Date: 20231222

ACTIVE INGREDIENTS: ALCOHOL 0.62 g/1 g
INACTIVE INGREDIENTS: GLYCERIN; ALOE VERA LEAF; WATER; ALPHA-TOCOPHEROL ACETATE

EMU HAND SANITIZER MIST SEA SALT

Purpose

Antiseptic, Hand Sanitizer

Drug Facts

This is a hand sanitizer manufactured according to the Temporary Policy for Preparation of Certain Alcohol-Based Hand Sanitizer Products During the Public Health Emergency (CoViD-19); Guidance for Industry.

The hand sanitizer is manufactured using only the following United States Pharmacopoeia (USP) grade ingredients in the preparation of the product (percentage in final product formulation) consistent with World Health Organization (WHO) recommendations:

1. Alcohol (ethanol) (USP or Food Chemical Codex (FCC) grade) (80%, volume/volume (v/v)) in an aqueous solution denatured according to Alcohol and Tobacco Tax and Trade Bureau regulations in 27 CFR part 20.
2. Glycerol (1.45% v/v).
3. Hydrogen peroxide (0.125% v/v).
4. Sterile distilled water or boiled cold water.

The firm does not add other active or inactive ingredients. Different or additional ingredients may impact the quality and potency of the product.

Active Ingredient | Purpose
Ethyl Alcohol 62% | Antiseptic

Use

Hand sanitizer to help reduce bacteria that can potentially cause disease. For use when soap and water are not available.

Warnings

For external use only. | Flammable. | Keep away from heat or flame. | Contents under pressure.

Do not use on children less than 2 months of age. Do not use on open skin wounds.

STOP USE

Stop using and ask a doctor if irritation or rash occurs.These may be signs of a serious condition.

When using this product keep out of eyes, ears and mouth. In case of contact with eyes, rinse eyes thoroughly with water.

Keep out of reach of children. If swallowed get medical help or contact a poison control center right away.

Directions

Place enough product on hands to cover all surfaces. Rub hands together until dry. Supervise children under 6 years of age to avoid swallowing.

Other information

Store between 15°-30° C (59°- 86°F)

Inactive ingredients

Aloe Barbadensis Leaf Juice, Fragrance, Glycerin, Purified Water, Tocopheryl Acetate

Questions or comments?

1-800-250-4643

Package Label - Principal Display Panel

Net Wt 2.2 FL OZ (62.4g) NDC: 80464-1006-1